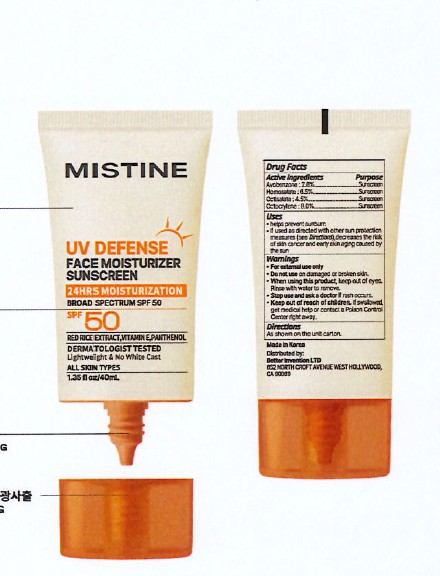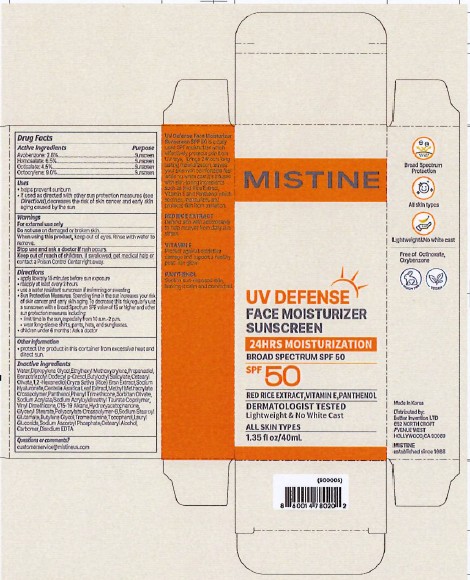 DRUG LABEL: MISTINE UV DEFENSE FACE MOISTURIZER SPF 50
NDC: 87458-004 | Form: CREAM
Manufacturer: BETTER INVENTION LTD
Category: otc | Type: HUMAN OTC DRUG LABEL
Date: 20260224

ACTIVE INGREDIENTS: OCTISALATE 4.5 mg/100 mL; HOMOSALATE 6.5 mg/100 mL; OCTOCRYLENE 9 mg/100 mL; AVOBENZONE 2.6 mg/100 mL
INACTIVE INGREDIENTS: 1,2-HEXANEDIOL; EDETATE DISODIUM; SODIUM ASCORBYL PHOSPHATE; CENTELLA ASIATICA LEAF; CARBOMER; BUTYLOCTYL SALICYLATE; SODIUM HYALURONATE; CETEARYL OLIVATE; ETHYLHEXYL METHOXYCRYLENE; PHENYL TRIMETHICONE; SORBITAN OLIVATE; DIPROPYLENE GLYCOL; WATER; CETEARYL ALCOHOL; GLYCERYL STEARATE; POLYACRYLATE CROSSPOLYMER-6; TROMETHAMINE; PROPANEDIOL; PANTHENOL; C15-19 ALKANE; HYDROXYACETOPHENONE; SODIUM STEAROYL GLUTAMATE; ORYZA SATIVA (RICE) BRAN; LAURYL GLUCOSIDE; BUTYLENE GLYCOL; TOCOPHEROL; BENZOTRIAZOLYL DODECYL P-CRESOL

MISTINE UV DEFENSE FACE MOISTURIZER SUNSCREEN SPF 50

Active Ingredients

Avobenzone: 2.6%
Homosalate: 6.5%
Octisalate:4.5%
Octocrylene: 9%

Purpose

Sunscreen

USES

- helps prevent sunburn
- If used as directed with other sun protection measures (see Directions), decreases the risj of skin cancer and early skin aging caused by the sun.

Warnings

For external use only

Do not use on damaged or broken skin

When using this product, keep out of eyes. Rinse with water to remove.

Stop use and ask a doctor if rash occurs.

Keep out of reach of children. If swallowed, get medical help or contact a Poison Control Center right away.

DIRECTIONS

- apply liberally 15 inches before sun exposure
- reapply at least every 2 hours
- use a water resistant sunscreen if swimming or sweating
- Sun Protection Measures. Spendin time in the sun increases your risk of skin cancer and early skin aging. To decrease this risk regularly use a susncreen with a Broad Spectrum SPF value of 15 or higher and other sun protection measures including:
- limit time in the sun especially from 10 a.m. - 2 p.m.
- wear long-sleeve shirts, pants, hats, and sunglasses
- children under 6 months: Ask a doctor

OTHER INFORMATION

- protect the product in this container from excessive heat and direct sun.

Inactive ingredients

Water, Dipropylene Glycol, Ethylhexyl Methoxycrylene, Propanediol, Benzotriazolyl Dodecyl p-Cresol, Butyloctyl Salicylate, Cetearyl Olivate, 1,2-Hexanediol, Methyl Methacrylate Crosspolymer, Panthenol, Phenyl Trimethicone, Sorbitan Olivate, Sodium Acrylate/Sodium Acryloyldimethyl Taurate Copolymer, Vinyl Dimethicone, C15-19 Alkane, Cetearyl Alcohol, Hydroxyacetophenone, Glyceryl Stearate, Polyacrylate Crosspolymer-6, Sodium Stearoyl Glutamate, Butylene Glycol, Carbomer, Tromethamine, Tocopherol, Oryza Sativa (Rice) Bran Extract, Sodium Hyaluronate, Lauryl Glucoside, Disodium EDTA, Centella Asiatica Leaf Extract, Sodium Ascorbyl Phosphate.

Questions or comments?

customerservice@mistineus.com